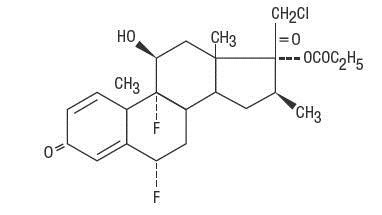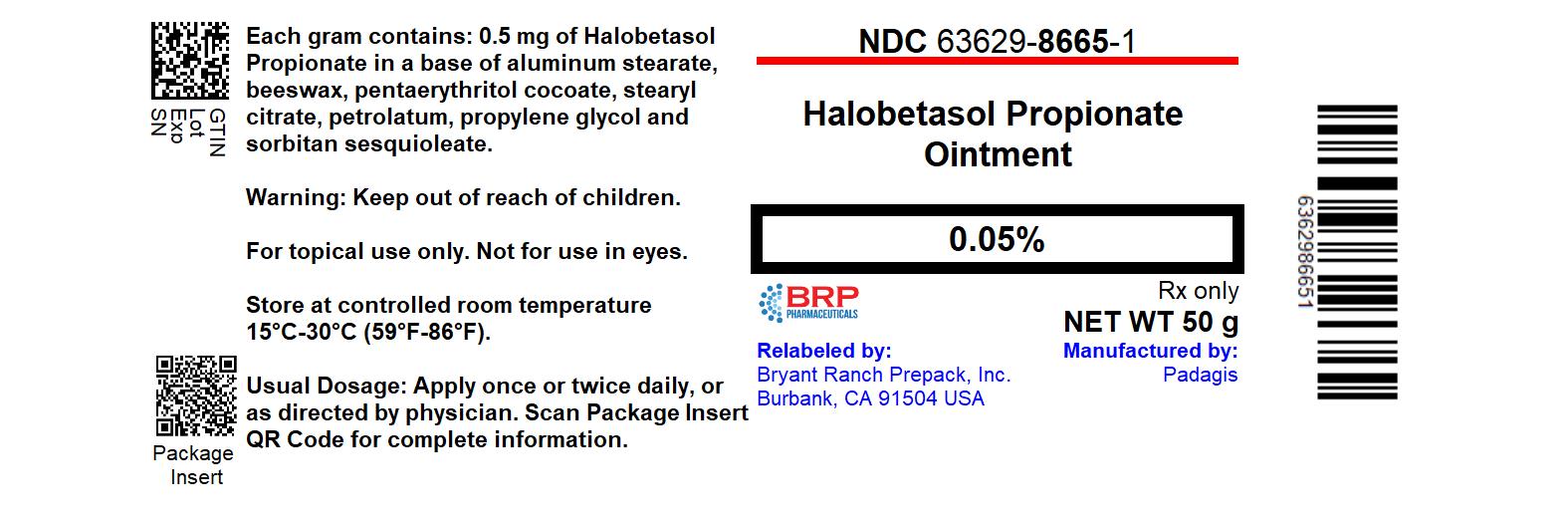 DRUG LABEL: Halobetasol Propionate
NDC: 63629-8665 | Form: OINTMENT
Manufacturer: Bryant Ranch Prepack
Category: prescription | Type: HUMAN PRESCRIPTION DRUG LABEL
Date: 20241024

ACTIVE INGREDIENTS: HALOBETASOL PROPIONATE 0.5 mg/1 g
INACTIVE INGREDIENTS: ALUMINUM STEARATE; YELLOW WAX; PETROLATUM; PROPYLENE GLYCOL; SORBITAN SESQUIOLEATE

HALOBETASOL PROPIONATE OINTMENT, 0.05%

For Dermatologic Use Only. Not for Ophthalmic Use.

Rx Only

DESCRIPTION

Halobetasol propionate ointment, 0.05% contains halobetasol propionate, a synthetic corticosteroid for topical dermatological use. The corticosteroids constitute a class of primarily synthetic steroids used topically as an anti-inflammatory and antipruritic agent.

Chemically halobetasol propionate is 21-chloro-6α, 9-difluoro-11β, 17-dihydroxy-16β-methylpregna-1, 4-diene-3-20-dione, 17-propionate, C25H31ClF2O5. It has the following structural formula:

Halobetasol propionate has the molecular weight of 485. It is a white crystalline powder insoluble in water.

Each gram of halobetasol propionate ointment, 0.05% contains 0.5 mg of halobetasol propionate in a base of aluminum stearate, beeswax, pentaerythritol cocoate, stearyl citrate, petrolatum, propylene glycol and sorbitan sesquioleate.

CLINICAL PHARMACOLOGY

Like other topical corticosteroids, halobetasol propionate has anti-inflammatory, antipruritic and vasoconstrictive actions.

The mechanism of the anti-inflammatory activity of the topical corticosteroids, in general, is unclear. However, corticosteroids are thought to act by the induction of phospholipase A2, inhibitory proteins, collectively called lipocortins. It is postulated that these proteins control the biosynthesis of potent mediators of inflammation such as prostaglandins and leukotrienes by inhibiting the release of their common precursor arachidonic acid. Arachidonic acid is released from membrane phospholipids by phospholipase A2.

Pharmacokinetics

The extent of percutaneous absorption of topical corticosteroids is determined by many factors including the vehicle and the integrity of the epidermal barrier. Occlusive dressings with hydrocortisone for up to 24 hours have not been demonstrated to increase penetration; however, occlusion of hydrocortisone for 96 hours markedly enhances penetration. Topical corticosteroids can be absorbed from normal intact skin. Inflammation and/or other disease processes in the skin may increase percutaneous absorption.

Human and animal studies indicate that less than 6% of the applied dose of halobetasol propionate enters the circulation within 96 hours following topical administration of the ointment.

Studies performed with halobetasol propionate ointment, 0.05% indicate that it is in the super-high range of potency as compared with other topical corticosteroids.

INDICATIONS AND USAGE

Halobetasol propionate ointment, 0.05% is a super-high potency corticosteroid indictated for the relief of the inflammatory and pruritic manifestations of corticosteroid-responsive dermatoses. Treatment beyond two consecutive weeks is not recommended, and the total dosage should not exceed 50 g/week because of the potential for the drug to suppress the hypothalamic-pituitary-adrenal (HPA) axis.

CONTRAINDICATIONS

Halobetasol propionate ointment, 0.05% is contraindicated in those patients with a history of hypersensitivity to any of the components of the preparation.

PRECAUTIONS

General

Systemic absorption of topical corticosteroids can produce reversible hypothalamic-pituitary-adrenal (HPA) axis suppression with the potential for glucocorticosteroid insufficiency after withdrawal of treatment. Manifestations of Cushing's syndrome, hyperglycemia, and glucosuria can also be produced in some patients by systemic absorption of topical corticosteroids while on treatment.

Patients applying a topical steroid to a large surface area or to areas under occlusion should be evaluated periodically for evidence of HPA axis suppression. This may be done by using the ACTH stimulation, A.M. plasma cortisol, and urinary free-cortisol tests. Patients receiving super potent corticosteroids should not be treated for more than 2 weeks at a time and only small areas should be treated at any one time due to the increased risk of HPA suppression.

Halobetasol propionate ointment, 0.05% produced HPA axis suppression when used in divided doses at 7 grams per day for one week in patients with psoriasis. These effects were reversible upon discontinuation of treatment.

If HPA axis suppression is noted, an attempt should be made to withdraw the drug, to reduce the frequency of application, or to substitute a less potent corticosteroid. Recovery of HPA axis function is generally prompt upon discontinuation of topical corticosteroids. Infrequently, signs and symptoms of glucocorticosteroid insufficiency may occur requiring supplemental systemic corticosteroids. For information on systemic supplementation, see prescribing information for those products.

Pediatric patients may be more susceptible to systemic toxicity from equivalent doses due to their larger skin surface to body mass ratios (see PRECAUTIONS: Pediatric Use_RefIDUSE).

If irritation develops, halobetasol propionate ointment, 0.05% should be discontinued and appropriate therapy instituted. Allergic contact dermatitis with corticosteroids is usually diagnosed by observing failure to heal rather than noting a clinical exacerbation as with most topical products not containing corticosteroids. Such an observation should be corroborated with appropriate diagnostic patch testing.

If concomitant skin infections are present or develop, an appropriate antifungal or antibacterial agent should be used. If a favorable response does not occur promptly, use of halobetasol propionate ointment, 0.05% should be discontinued until the infection has been adequately controlled.

Halobetasol propionate ointment, 0.05% should not be used in the treatment of rosacea or perioral dermatitis, and it should not be used on the face, groin, or in the axillae.

Information for Patients

Patients using topical corticosteroids should receive the following information and instructions:

1. The medication is to be used as directed by the physician. It is for external use only. Avoid contact with the eyes.
2. The medication should not be used for any disorder other than that for which it was prescribed.
3. The treated skin area should not be bandaged, or otherwise covered or wrapped, so as to be occlusive unless directed by the physician.
4. Patients should report to their physician any signs of local adverse reactions.
5. Parents of pediatric patients should be advised not to use tight-fitting diapers or plastic pants on a child being treated in the diaper area, as these garments may constitute occlusive dressing.

Laboratory Tests

The following tests may be helpful in evaluating patients for HPA axis suppression: ACTH-stimulation test; A.M. plasma-cortisol test; Urinary free-cortisol test.

Carcinogenesis, Mutagenesis, Impairment of Fertility

Long-term animal studies have not been performed to evaluate the carcinogenic potential of halobetasol propionate.

Positive mutagenicity effects were observed in two genotoxicity assays. Halobetasol propionate was positive in a Chinese hamster micronucleus test, and in a mouse lymphoma gene mutation assay in vitro.

Studies in the rat following oral administration at dose levels up to 50 µg/kg/day indicated no impairment of fertility or general reproductive performance.

In other genotoxicity testing, halobetasol propionate was not found to be genotoxic in the Ames/Salmonella assay, in the sister chromatid exchange test in somatic cells of the Chinese hamster, in chromosome aberration studies of germinal and somatic cells of rodents, and in a mammalian spot test to determine point mutations.

Pregnancy

Teratogenic effects:

Pregnancy Catergory C:

Corticosteroids have been shown to be teratogenic in laboratory animals when administered systemically at relatively low dosage levels. Some corticosteroids have been shown to be teratogenic after dermal application in laboratory animals.

Halobetasol propionate has been shown to be teratogenic in SPF rats and chinchilla-type rabbits when given systemically during gestation at doses of 0.04 to 0.1 mg/kg in rats and 0.01 mg/kg in rabbits. These doses are approximately 13, 33 and 3 times, respectively, the human topical dose of halobetasol propionate ointment, 0.05%. Halobetasol propionate was embryotoxic in rabbits but not in rats.

Cleft palate was observed in both rats and rabbits. Omphalocele was seen in rats, but not in rabbits.

There are no adequate and well-controlled studies of teratogenic potential of halobetasol propionate in pregnant women. Halobetasol propionate ointment, 0.05% should be used during pregnancy only if the potential benefit justifies the potential risk to the fetus.

Nursing Mothers

Systemically administered corticosteroids appear in human milk and could suppress growth, interfere with endogenous corticosteroid production, or cause other untoward effects. It is not known whether topical administration of corticosteroids could result in sufficient systemic absorption to produce detectable quantities in human milk. Because many drugs are excreted in human milk, caution should be exercised when halobetasol propionate ointment, 0.05% is administered to a nursing woman.

Pediatric Use

Safety and effectiveness of halobetasol propionate ointment, 0.05% in pedriatric patients have not been established and use in pediatric patients under 12 is not recommended. Because of a higher ratio of skin surface area to body mass, pediatric patients are at a greater risk than adults of HPA suppression and Cushing's syndrome when they are treated with topical corticosteroids. They are therefore also at greater risk of adrenal insufficiency during or after withdrawal of treatment. Adverse effects including striae have been reported with inappropriate use of topical corticosteroids in infants and children.

HPA axis suppression, Cushing's syndrome, linear growth retardation, delayed weight gain and intracranial hypertension have been reported in children receiving topical corticosteroids. Manifestations of adrenal suppression in children include low plasma cortisol levels and an absence of response to ACTH stimulation. Manifestations of intracranial hypertension include bulging fontanelles, headaches, and bilateral papilledema.

Geriatric Use

Of approximately 400 patients treated with halobetasol propionate ointment, 0.05% in clinical studies, 25% were 61 years and over and 6% were 71 years and over. No overall differences in safety or effectiveness were observed between these patients and younger patients; and other reported clinical experience has not identified differences in responses between the elderly and younger patients, but greater sensitivity of some older individuals cannot be ruled out.

ADVERSE REACTIONS

In controlled clinical trials, the most frequent adverse events reported for halobetasol propionate ointment, 0.05% included stinging or burning in 1.6% of the patients. Less frequently reported adverse reactions were pustulation, erythema, skin atrophy, leukoderma, acne, itching, secondary infection, telangiectasia, urticara, dry skin, miliaria, paresthesia, and rash.

The following additional local adverse reactions are reported infrequently with topical corticosteroids, and they may occur more frequently with high potency corticosteroids, such as halobetasol propionate ointment, 0.05%. These reactions are listed in an approximate decreasing order of occurrence: folliculitis, hypertrichosis, acneiform eruptions, hypopigmentation, perioral dermatitis, allergic contact dermatitis, secondary infection, striae and miliaria.

OVERDOSAGE

Topically applied halobetasol propionate ointment, 0.05% can be absorbed in sufficient amounts to produce systemic effects (see PRECAUTIONS).

DOSAGE AND ADMINISTRATION

Apply a thin layer of halobetasol propionate ointment, 0.05% to the affected skin once or twice daily, as directed by your physician, and rub in gently and completely.

Halobetasol propionate ointment, 0.05% is a high potency topical corticosteroid; therefore, treatment should be limited to two weeks, and amounts greater than 50g/wk should not be used. As with other corticosteroids, therapy should be discontinued when control is achieved. If no improvement is seen within 2 weeks, reassessment of diagnosis may be necessary.

Halobetasol propionate ointment, 0.05% should not be used with occlusive dressings.

HOW SUPPLIED

Halobetasol propionate ointment, 0.05% is supplied in the following tube sizes:

- 50 g (NDC 63629-8665-1)

STORAGE

Store between 15°C and 30°C (59°F and 86°F).

Repackaged/Relabeled by:
Bryant Ranch Prepack, Inc.
Burbank, CA 91504

Manufactured By Padagis®

Yeruham, Israel

Distributed By Padagis®

Allegan, MI 49010

www.padagis.com

Rev 12-22

9R500 RC PH4

PACKAGE LABEL

Halobetasol Propionate 0.05% Ointment